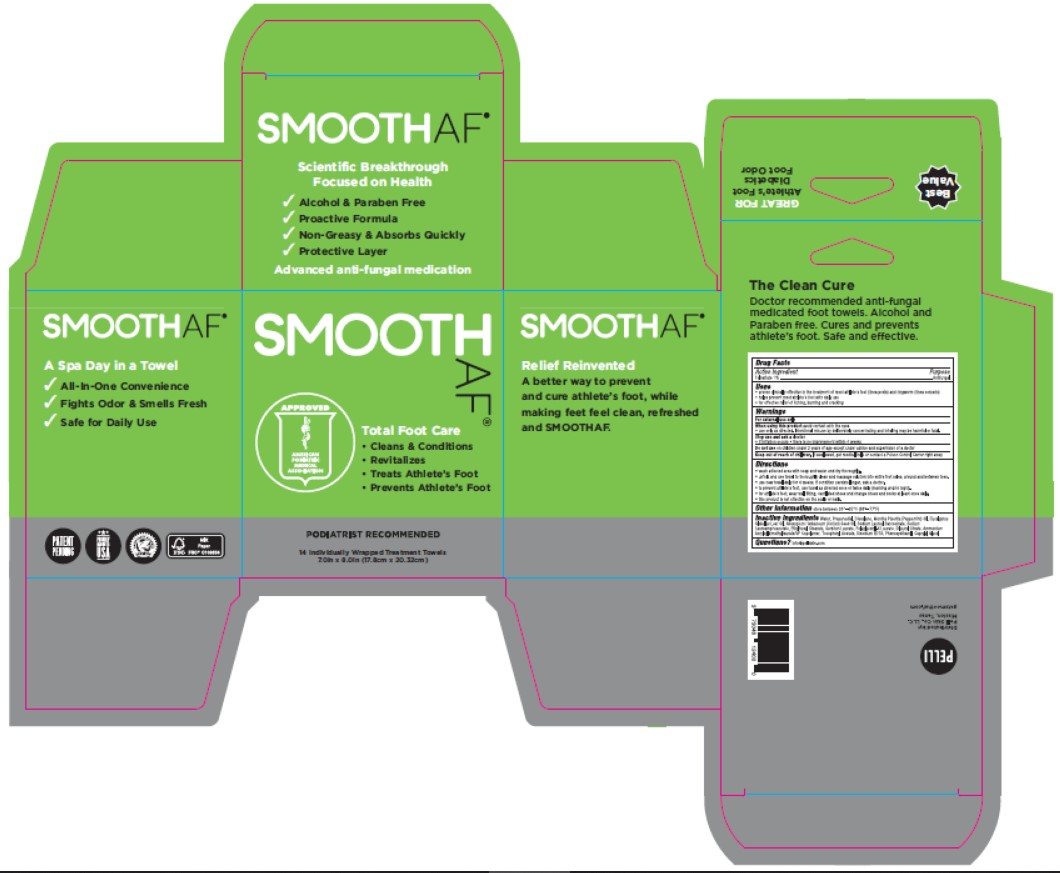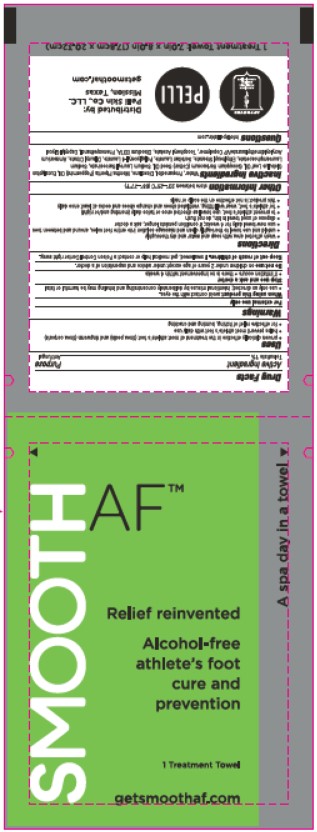 DRUG LABEL: Smooth AF
NDC: 73046-124 | Form: CLOTH
Manufacturer: Pelli Skin Co.,LLC.
Category: otc | Type: HUMAN OTC DRUG LABEL
Date: 20251009

ACTIVE INGREDIENTS: TOLNAFTATE 1 g/100 g
INACTIVE INGREDIENTS: CAPRYLYL GLYCOL; SODIUM LAUROYL SARCOSINATE; WATER; PROPANEDIOL; DIOXOLANE; DISODIUM LAUROAMPHODIACETATE; SODIUM LAURATE; COTTONSEED OIL; PEPPERMINT OIL; .ALPHA.-TOCOPHEROL ACETATE; AMMONIUM ACRYLOYLDIMETHYLTAURATE/VP COPOLYMER; ETHYLHEXYL STEARATE; EDETATE DISODIUM ANHYDROUS; EUCALYPTUS OIL; DILAURYL CITRATE; PHENOXYETHANOL

Alcohol- Free
Athlete's Foot

Active Ingredient

Tolnaftate 1%

Purpose

Antifungal

Uses

• proven clinically effective in the treatment of most athlete's foot 9tinea pedis) and ringworm (tinea corporis)

• helps prevent most athlete's foot with daily use

• for effective relief of itching, burning and cracking

Warnings

For external use only

Directions

• wash affected area with soap and water and dry thoroughly

• unfold and use towel to thoroughly clean and massage solution into entire foot soles, around and between toes

• sue new towel daily for 4 weeks; if condition persists longer, ask a doctor

• dispose of uses towel in bin, do not flush

• to prevent athlete's foot, use towel as directed once or twice daily (morning and/or night)

• for athlete's foot, wear well fitting, ventilated shoes and change shoes and socks at least once daily

• this product is not effective on the scalp or nails

When using this product avoid contact with the eyes.

• use only as directed; intentional misuse by deliberately concentrating and inhaling may harmful or fatal

Stop use and ask a doctor

• if irritation occurs • there is no improvement within 4 weeks

Do not use on children under 2 years of age except under advice and supervision of a doctor.

Other information

Store between 20°–25°C (68°–77°F)

Keep out of reach of children

If swallowed, get medical help or contact a Poison Control Center right away.

Inactive ingredients

Water, Propanediol, Dioxolane, Mentha Piperita (Peppermint) Oil, Eucalyptus Globulus Leaf Oil, Gossypium Herbaceum (Cotton) Seed Oil, Sodium Lauroyl Sarcosinate, Sodium Lauroamphoacetate, Ethylhexyl Stearate, Sorbitan Laurate, Polyglyceryl-4 Laurate, Dilauryl Citrate, Ammonium Acryloyldimethyltaurate/VP Copolymer, Tocopheryl Acetate, Disodium EDTA, Phenoxyethanol, Caprylyl Glycol

Questions

info@pelliskin.com

Label

SMOOTH

AFTM

Relief reinvented

Alcohol-free

athlete's foot

cure and

prevention

1 Treatment towel

getsmoothaf.com

A spa day in a towel

APPROVED

AMERICAN PODIATRIC

MEDICAL

ASSOCIATION

PELLI

Distributed by:

Pelli Skin Co., LLC.

Mission, Texas

getsmoothaf.com

1 Treatment Towel: 7.0in x 8.0in (17.8cm x 20.32cm)

A spa day in a towel

- All-In-One Convenience
- Fights Odor & Smells Fresh
- Safe for Daily Use

Scientific Breakthrough Focused on Health

- Alcohol & Paraben Free
- Proactive Formula
- Non-Greasy & Absorbs Quickly

Proactive Layer

Advanced anti-fungal medication

Total Foot Care

- Cleans & Conditions
- Revitalizes
- Treats Athlete's Foot
- Prevents Athlete's Foot

The Clean Cure

Doctor recommended anti-fungal

medicated foot towels. Alcohol and

Paraben free. Cures and prevents

Athlete's Foot. Safe and effective.

GREAT FOR

Athlete's foot

Diabetics

Foot Odor

PATENT

PENDING

PROUDLY

MADE IN THE

USA

RAINFOREST ALLIANCE

CERTIFIED

MIX Paper

FSC FSCR C109834

PODIATRIST RECOMMENDED

14 Individually Wrapped Treatment Towels

7.0in x 8.0in (17.8cm x 20.32cm)